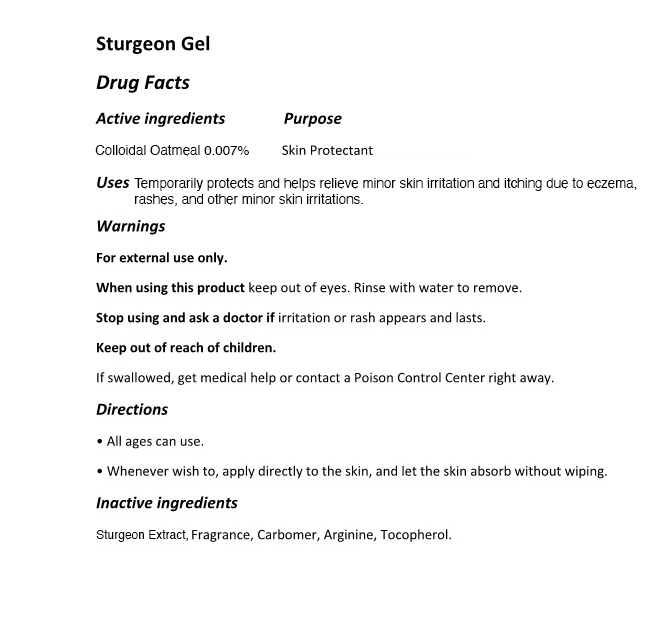 DRUG LABEL: The Zoeun Skin Sturgeon Gel
NDC: 83636-123 | Form: GEL
Manufacturer: Sturgeonbio Co.,Ltd.
Category: otc | Type: HUMAN OTC DRUG LABEL
Date: 20251001

ACTIVE INGREDIENTS: OATMEAL 0.007 g/100 mL
INACTIVE INGREDIENTS: STURGEON, UNSPECIFIED; CARBOMER HOMOPOLYMER, UNSPECIFIED TYPE; TOCOPHEROL; ARGININE; FRAGRANCE 13576

123 THE ZOEUN SKIN STURGEON GEL

Active Ingredients 0.007%

Colloidal Oatmeal 0.007%

Purpose

Skin Protectant

Uses

Temporarily protects and helps relieve minor skin irritation and itching due to eczema, rashes, insect bites, and other minor skin irritations.

Warnings

- Keep out of reach of children.
- If swallowed, get medical help or contact a Poison Control Center right away.

Warnings

Stop using and ask a doctor if irritation or rash appears and lasts.

Warnings

- When using this product keep out of eyes.
- Rinse with water to remove.

Warnings

For external use only.

Directions

- All ages can use.
- Whenever wish to, apply directly to the skin, and let the skin absorb without wiping.

Inactive ingredients

Sturgeon Extract, Fragrance, Carbomer, Arginine, Tocopherol.